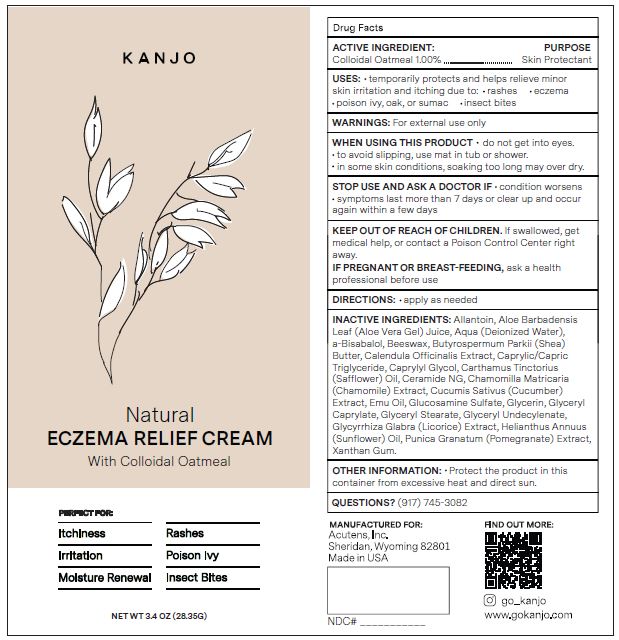 DRUG LABEL: ECZEMA RELIEF
NDC: 80551-301 | Form: CREAM
Manufacturer: ACUTENS, INC.
Category: otc | Type: HUMAN OTC DRUG LABEL
Date: 20230925

ACTIVE INGREDIENTS: OATMEAL 1 g/100 g
INACTIVE INGREDIENTS: SHEA BUTTER; ALLANTOIN; ALOE VERA LEAF; WATER; .ALPHA.-BISABOLOL, (+)-; CHAMOMILE; GLUCOSAMINE SULFATE; GLYCERYL CAPRYLATE; SUNFLOWER OIL; XANTHAN GUM; CUCUMBER; EMU OIL; GLYCERIN; GLYCERYL MONOSTEARATE; GLYCERYL 1-UNDECYLENATE; LICORICE; POMEGRANATE; CERAMIDE NG; CALENDULA OFFICINALIS WHOLE; MEDIUM-CHAIN TRIGLYCERIDES; CAPRYLYL GLYCOL; SAFFLOWER OIL; YELLOW WAX

ACUTENS - KANJO - NATURAL ECZEMA RELIEF CREAM

ACTIVE INGREDIENTS

Colloidal Oatmeal 1.00%

PURPOSE

SKIN PROTECTANT

USES

- temporarily protects and helps relieve minor skin irritation and itching due to:
- rashes
- eczema
- poison ivy, oak, or sumac
- insect bites

WARNINGS

- do not get into eyes.
- to avoid slipping, use mat in tub or shower.
- in some skin conditions, soaking too long may over dry.

STOP USE AND ASK A DOCTOR IF

- condition worsens
- symptoms last more than 7 days or clear up and occur again within a few days

KEEP OUT OF REACH OF CHILDREN. If swallowed, get medical help, or contact a Poison Control Center right away.

PREGNANCY

IF PREGNANT OR BREAST-FEEDING, ask a health professional before use

DIRECTIONS

- apply as needed

INACTIVE INGREDIENTS

Allantoin, Aloe Barbadensis Leaf (Aloe Vera Gel) Juice, Aqua (Deionized Water), a-Bisabalol, Beeswax, Butyrospermum Parkii (Shea) Butter, Calendula Officinalis Extract, Caprylic/Capric Triglyceride, Caprylyl Glycol, Carthamus Tinctorius (Safflower) Oil, Ceramide NG, Chamomilla Matricaria (Chamomile) Extract, Cucumis Sativus (Cucumber) Extract, Emu Oil, Glucosamine Sulfate, Glycerin, Glyceryl Caprylate, Glyceryl Stearate, Glyceryl Undecylenate, Glycyrrhiza Glabra (Licorice) Extract, Helianthus Annuus
(Sunflower) Oil, Punica Granatum (Pomegranate) Extract, Xanthan Gum.

OTHER INFORMATION

Protect the product in this container from excessive heat and direct sun.

QUESTIONS?

(917) 745-3082